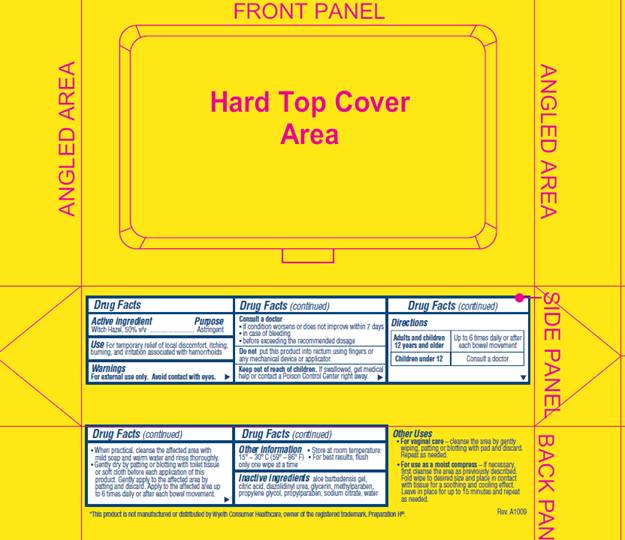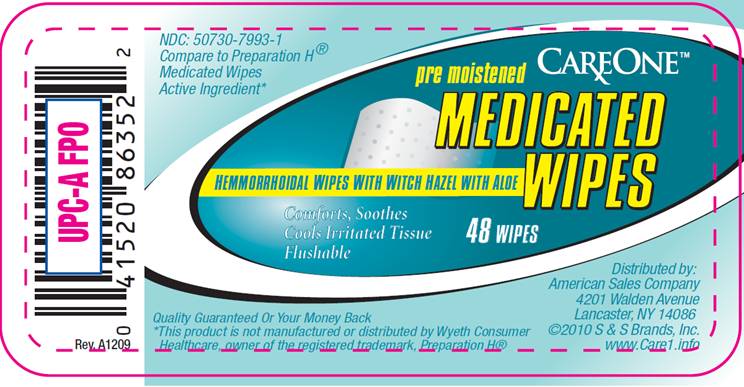 DRUG LABEL: Medicated Wipes
NDC: 50730-7993 | Form: SOLUTION
Manufacturer: Triad Group
Category: otc | Type: HUMAN OTC DRUG LABEL
Date: 20100415

ACTIVE INGREDIENTS: witch hazel 0.50 mL/1 mL
INACTIVE INGREDIENTS: aloe vera leaf; citric acid monohydrate; diazolidinylurea; glycerin; methylparaben; propylene glycol; propylparaben; sodium citrate; water

DRUG FACTS

ACTIVE INGREDIENT

Witch Hazel 50% v/v

PURPOSE

Astringent

USE

For temporary relief of local discomfort, burning, and irritation associated with hemorrhoids

WARNINGS

For external use only. Avoid contact with eyes.

Consult a doctor

- if condition worsens or does not improve within 7 days
- in case of bleeding
- before exceeding the recommended dosage

Do not

put this product into rectum using fingers or any mechanical device or applicator

Keep out of reach of children

If swallowed, get medical help or contact a Poison Control Center right away.

DIRECTIONS

Adults and children 12 years and older | Up to 6 times daily or after each bowel movement
Children under 12 | Consult a doctor

- When practical, cleanse the affected area with mild soap and warm water and rinse thoroughly.
- Gently dry by patting or blotting with toilet tissue or soft cloth before each application of this product. Gently apply to the affected area by patting and then discard. Apply to the affected area up to 6 times daily or after each bowel movement.

OTHER INFORMATION

- Store at room temperature: 15°- 30° C (59° - 86° F)
- For best results, flush only one wipe at a time

OTHER USES

- for vaginal care - cleanse the area by gently wiping, patting or blotting with pad and discard. Repeat as needed.
- for use as a moist compress - if necessary, first cleanse the area as previously described. Fold wipe to desired size and place in contact with tissue for a soothing and cooling effect. Leave in place for up to 15 minutes and repeat as needed.

INACTIVE INGREDIENTS

aloe barbadensis gel, citric acid, diazolidinyl urea, glycerin, methylparaben, propylene glycol, propylparaben, sodium citrate, water

PACKAGE INFORMATION - LABEL

NDC 50730-7993-1
Compare to Preparation H® active ingredient*

CAREONE®
pre-moistened
MEDICATED WIPES
HEMORRHOIDAL WIPES WITH WITCH HAZEL WITH ALOE
Comforts, Soothes
Cools Irritated Tissue
Flushable

48 WIPES

Distributed by:
American Sales Company
4201 Walden Avenue
Lancaster, NY, 14086

©2010 S and S Brands, Inc,
www.Care1.info

Quality Guaranteed or your money back.

*This product is not manufactured or distributed by Wyeth Consumer Healthcare, owner of the registered trademark PREPARATION H®.